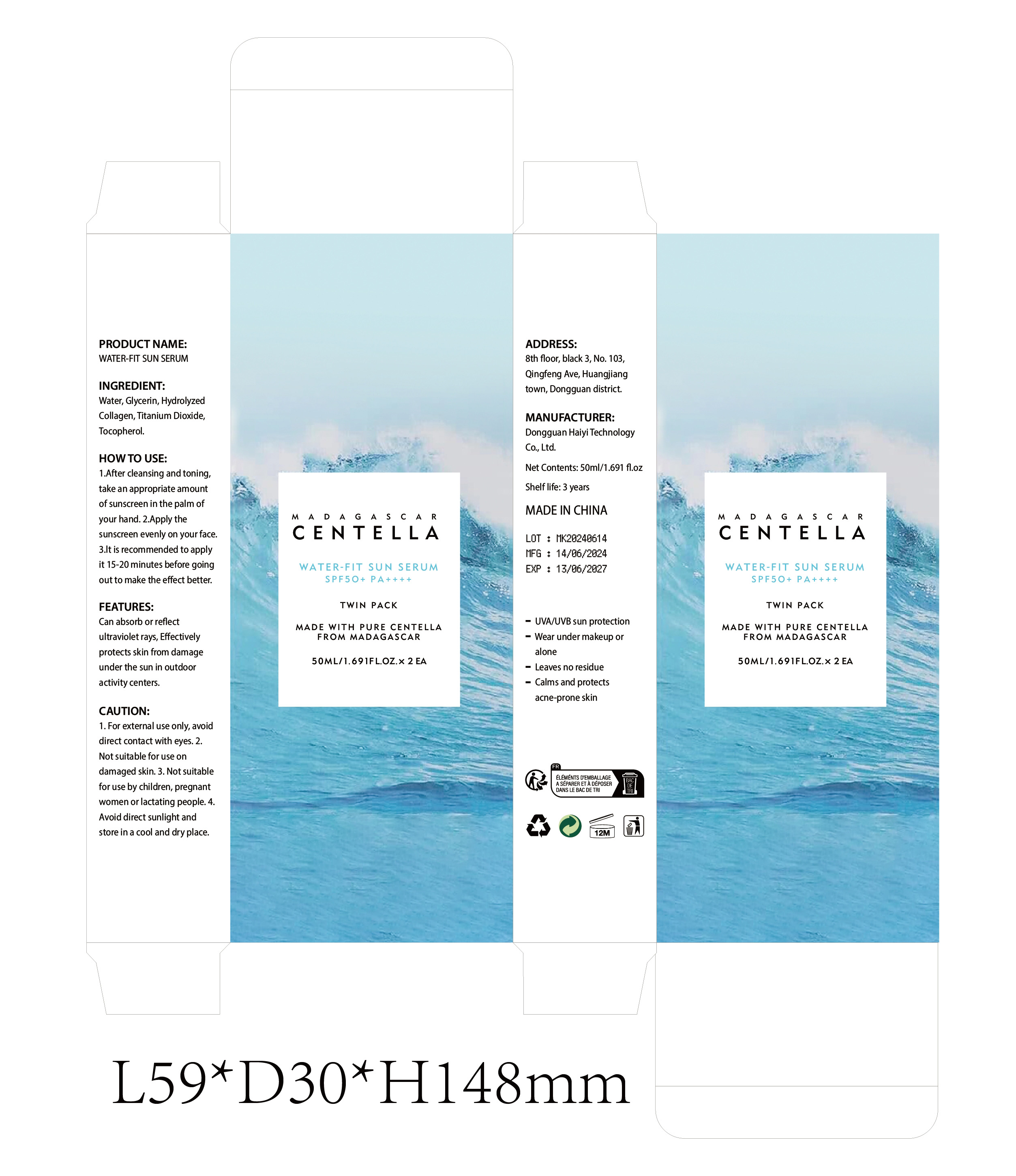 DRUG LABEL: WATER-FIT SUN SERUM
NDC: 84732-009 | Form: CREAM
Manufacturer: Dongguan Haiyi Technology Co.,Ltd.
Category: otc | Type: HUMAN OTC DRUG LABEL
Date: 20240924

ACTIVE INGREDIENTS: WATER 1 mg/50 mL
INACTIVE INGREDIENTS: GLYCERIN; TITANIUM DIOXIDE; TOCOPHEROL; COLLAGEN ALPHA-1(I) CHAIN BOVINE

Active ingredient

Water

Inactive ingredient

Glycerin, Hydrolyzed Collagen, Titanium Dioxide,Tocopherol.

Purpose section

Can absorb or reflectultraviolet rays, Effectively protects skin from damage under the sun in outdoor activity centers.

Warning

1. For external use only, avoiddirect contact with eyes.

2.Not suitable for use ondamaged skin.

3. Not suitablefor use by children, pregnantwomen or lactating people.

4.Avoid direct sunlight andstore in a cool and dry place.

stop use

Not suitable for use on damaged skin.

not use

Not suitable for use by children, pregnantor breastfeeding people.

OUT OF CHILDREN

KEEP THE PRODUCT OUT OF REACH OF CHILDREN to

HOW TO USE

1.After cleansing and toning,take an appropriate amount of sunscreen in the palm of your hand.

2.Apply the sunscreen evenly on your face.

3.lt is recommended to applyit 15-20 minutes before going out to make the effect better.

Dosage

Once a day when the sun comes out